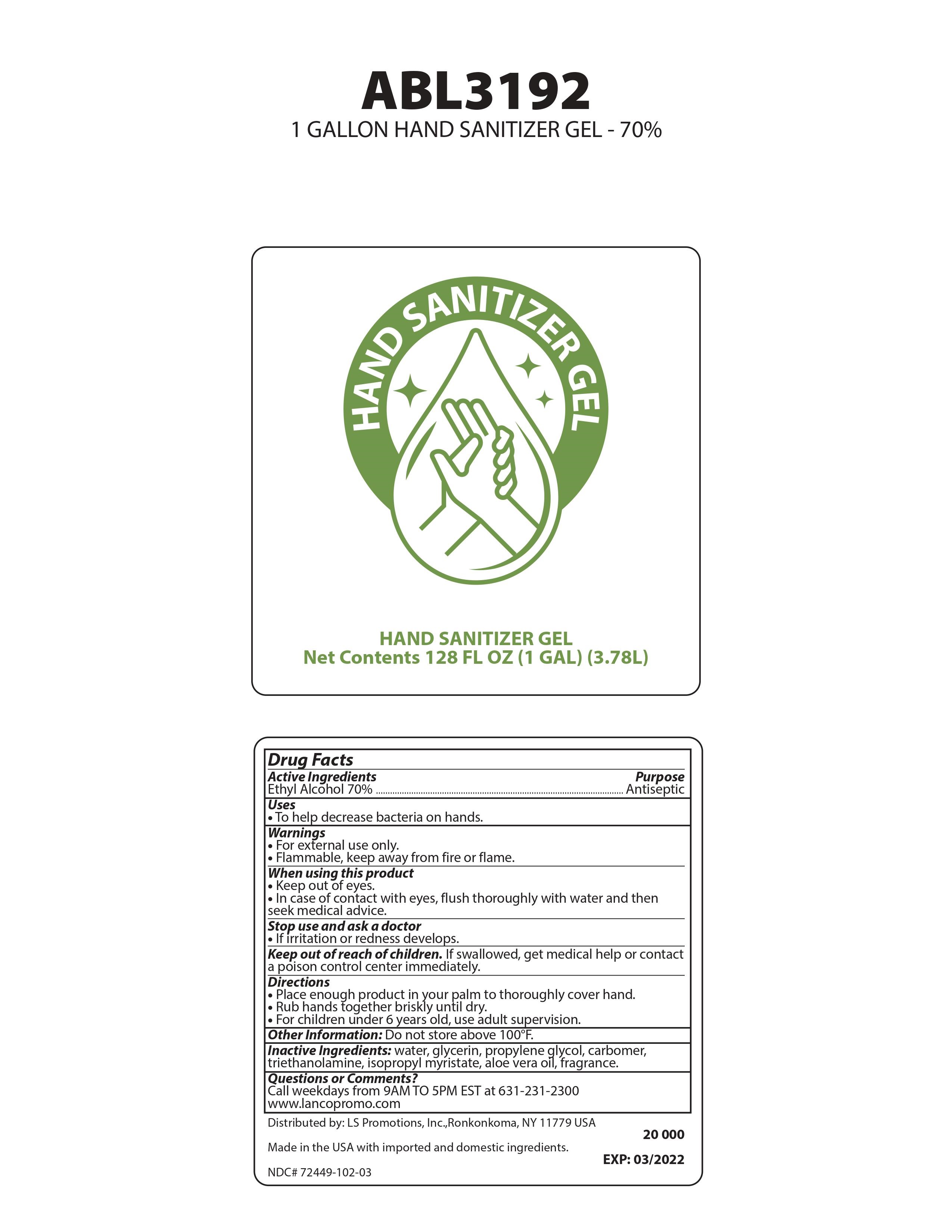 DRUG LABEL: Hand Sanitizer Gel
NDC: 72449-102 | Form: GEL
Manufacturer: LS Promotions Inc.
Category: otc | Type: HUMAN OTC DRUG LABEL
Date: 20200507

ACTIVE INGREDIENTS: ALCOHOL 70 mL/100 mL
INACTIVE INGREDIENTS: TROLAMINE; ALOE VERA WHOLE; GLYCERIN; CARBOMER 1342; WATER; ISOPROPYL MYRISTATE; PROPYLENE GLYCOL

Hand Sanitizer Gel 70%

Drug Facts

Active Ingredients

Ethyl Alcohol

Purpose

Antiseptic

Uses

- To help decrease bacteria on hands.

Warnings

- For external use only.
- Flammable, keep away from fire or flame

When using this product

- Keep out of eyes.
- In case of contact with eyes, flush thoroughly with water and then seek medical advise.

Stop use and ask a doctor

- If irritation or redness develops

Keep out of reach of children

- If swallowed, get medical help or contact a poison control center immediately.

Directions

- Place enough product in your palm to thoroughly cover hand.
- Rub hands together briskly until dry.
- For children under 6 years old, use adult supervision.

Other information

- Do not store above 100°F

Inactive ingredients

Water, Glycerin, Propylene Glycol, Carbomer, Triethanolamine, Isopropyl Myristate, Aloe Vera Oil, Fragrance.

Questions or Comments

Call weekdays from 9 AM to 5 PM EST at 631-231-2300 - www.lancopromo.com

Package Label - Principal Display Panel

ABL3192 - Hand Sanitizer Gel NDC 72449-102-03